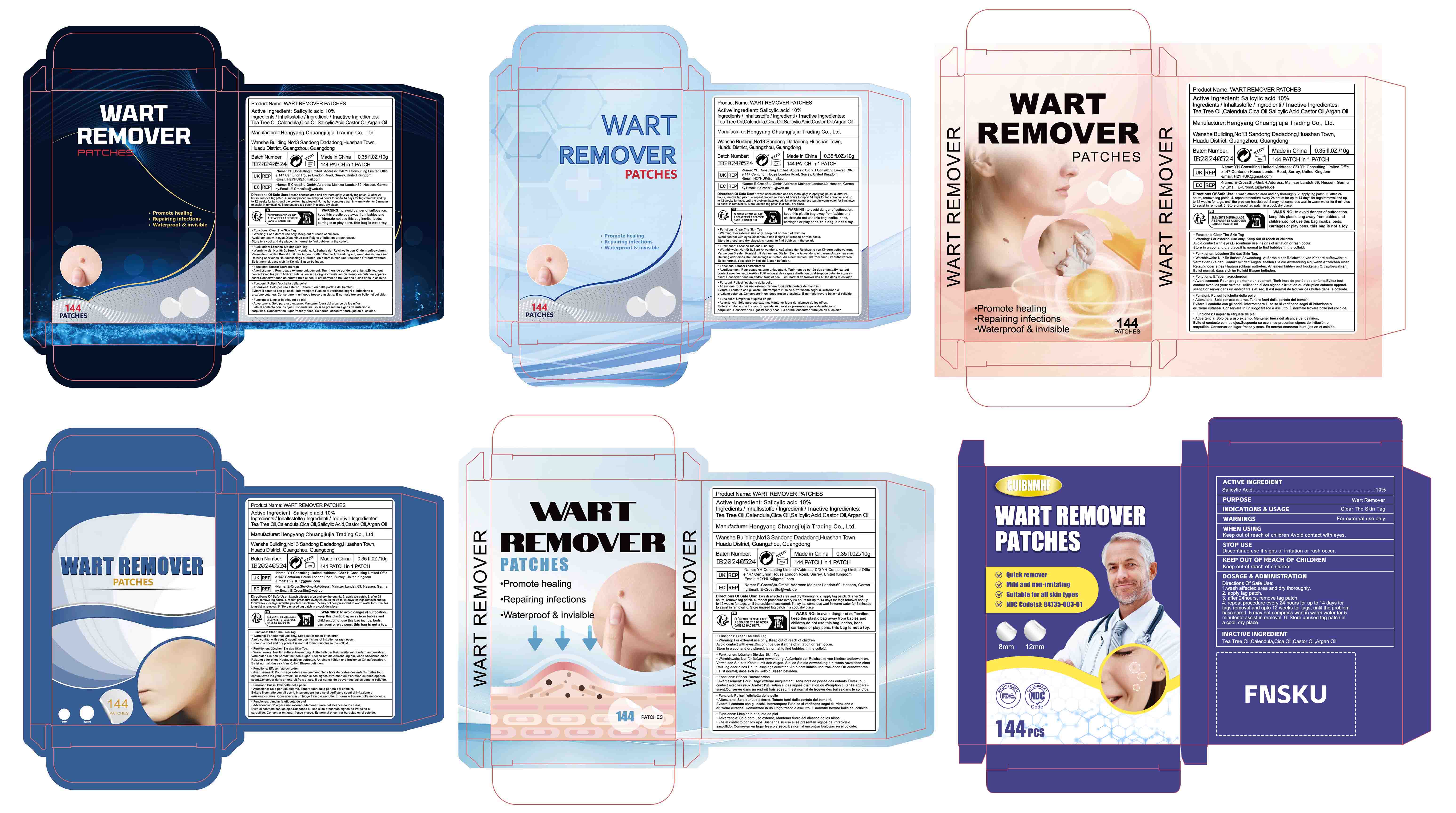 DRUG LABEL: WART REMOVER PATCHES
NDC: 84735-003 | Form: PATCH
Manufacturer: Hengyang Chuangjiujia Trading Co., Ltd.
Category: otc | Type: HUMAN OTC DRUG LABEL
Date: 20250722

ACTIVE INGREDIENTS: SALICYLIC ACID 0.1 g/1 1
INACTIVE INGREDIENTS: TEA TREE OIL; CALENDULA OFFICINALIS FLOWER; CASTOR OIL; ARGAN OIL; CENTELLA ASIATICA

WART REMOVER PATCHES

ACTIVE INGREDIENT

Salicylic Acid 10%

PURPOSE

WART REMOVER

INDICATIONS AND USAGE

Clear The Skin Tag

WARNINGS

For external use only.

Keep out of reach of children Avoid contact with eyes.

STOP USE

Discontinue use if signs of irritation or rash occur.

Keep out of reach of children

DOSAGE AND ADMINISTRATION

Directions Of Safe Use: 1.wash affected area and dry thoroughly. 2. apply tag patch. 3. after 24hours, remove tag patch. 4. repeat procedure every 24 hours for up to 14 days for tags removal and upto 12 weeks for tags, until the problem hascleared. 5.may hot compress wart in warm water for 5 minutesto assist in removal. 6. Store unused tag patch in a cool, dry place.

INACTIVE INGREDIENT

Tea Tree Oil
Calendula
Cica Oil
Castor Oil
Argan Oil